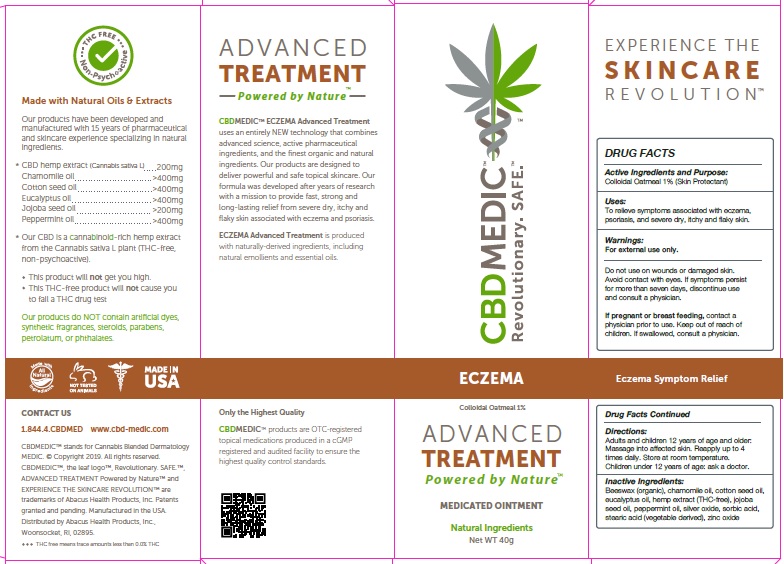 DRUG LABEL: CBDMEDIC Eczema
NDC: 24909-730 | Form: OINTMENT
Manufacturer: AIDANCE SKINCARE & TOPICAL SOLUTIONS, LLC
Category: otc | Type: HUMAN OTC DRUG LABEL
Date: 20190306

ACTIVE INGREDIENTS: OATMEAL 10 mg/1 g
INACTIVE INGREDIENTS: WHITE WAX; CHAMAEMELUM NOBILE FLOWER OIL; COTTONSEED OIL; EUCALYPTUS OIL; HEMP; JOJOBA OIL; PEPPERMINT OIL; SILVER OXIDE; SORBIC ACID; STEARIC ACID; ZINC OXIDE

CBDMEDIC Eczema

Active Ingredients and Purpose

Colloidal Oatmeal 1% (Skin Protectant)

Uses

To relieve symptoms associated with eczema, psoriasis, and severe dry, itchy and flaky skin.

Warnings

For external use only. Do not use on wounds or damaged skin. Avoid contact with eyes. If symptoms persist for more than seven days, discontinue use and consult a physician.

KEEP OUT OF REACH OF CHILDREN

If pregnant or breast feeding, contact a physician prior to use. Keep out of reach of children. If swallowed, consult a physician.

Directions:

Adults and children 12 years of age and older: Massage into affected skin. Reapply up to 4 times daily. Store at room temperature.
Children under 12 years of age: ask a doctor.

Inactive ingredients

Beeswax (organic), chamomile oil, cotton seed oil, eucalyptus oil, hemp extract (THC-free), jojoba seed oil, peppermint oil, silver oxide, sorbic acid, stearic acid (vegetable derived), zinc oxide.